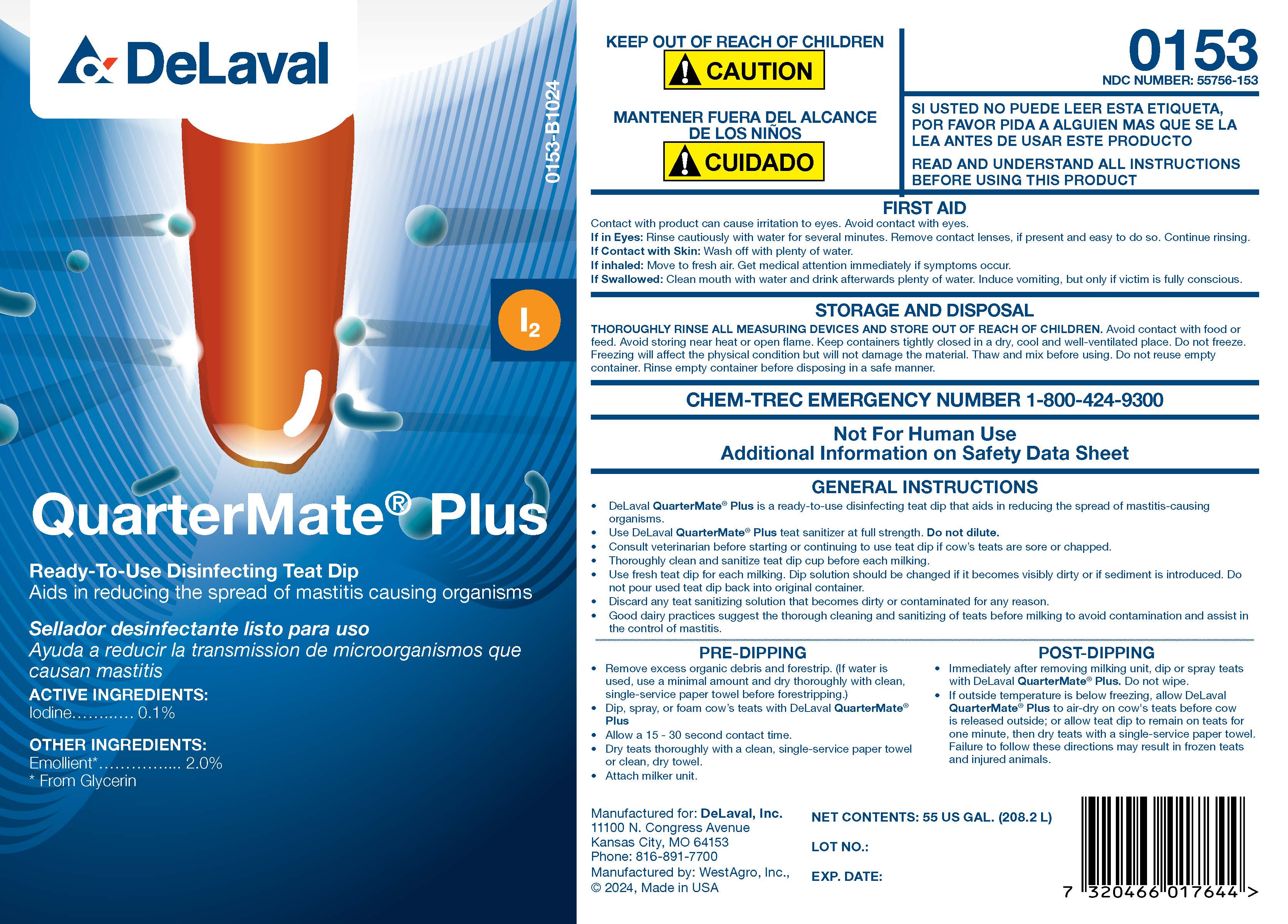 DRUG LABEL: QuarterMate
NDC: 55756-153 | Form: SOLUTION
Manufacturer: DeLaval
Category: animal | Type: OTC ANIMAL DRUG LABEL
Date: 20241021

ACTIVE INGREDIENTS: Iodine 0.1 kg/100 kg
INACTIVE INGREDIENTS: SODIUM HYDROXIDE; ANHYDROUS CITRIC ACID; POLOXAMER 335; GLYCERIN; XANTHAN GUM; POLOXAMER 403; water; SODIUM CHLORIDE; SODIUM IODIDE; DOCUSATE SODIUM; SODIUM IODATE

DeLaval QuarterMate Plus

Ready-To-Use Disinfecting Teat Dip

Aids in reducing the spread of mastitis causing organisms

ACTIVE INGREDIENTS:

Iodine ........................................... 0.1%

OTHER INGREDIENTS:

Emollient*..................2.0%

* From Glycerin

KEEP OUT OF REACH OF CHILDREN

! CAUTION

READ AND UNDERSTAND ALL INSTRUCTIONS BEFORE USING THIS PRODUCT

FIRST AID

Contact with product can cause irritation to eyes. Avoid contact with eyes.

If in Eyes: Rinse cautiously with water for several minutes. Remove contact lenses, if present and easy to do. Continue rinsing.

If Contact with Skin: Wash off with plenty of water.

If inhaled: Move to fresh air. Get medical attention immediately if symptoms occur.

If Swallowed: Clean mouth with water and drink afterwards plenty of water. Induce vomiting, but only if victim is fully conscious.

STORAGE AND HANDLING

STORAGE AND DISPOSALTHOROUGHLY RINSE ALL MEASURING DEVICES AND STORE OUT OF REACH OF CHILDREN. Avoid contact with food or feed. Avoid storing near heat or open flame. Keep containers tightly closed in a dry, cool and well-ventilated place. Do not freeze. Freezing will affect the physical condition but will not damage the material. Thaw and mix before using. Do not reuse empty container. Rinse empty container before disposing in a safe manner.

CHEM-TREC EMERGENCY NUMBER 1-800-424-9300

Not For Human Use

Additional Information on Safety Data Sheet

GENERAL INSTRUCTIONS

- DeLaval QuarterMate® Plus is a ready-to-use disinfecting teat dip that aids in reducing the spread of mastitis-causing organisms.
- Use DeLaval QuarterMate® Plus teat sanitizer at full strength. Do not dilute.
- Consult veterinarian before starting or continuing to use teat dip if cow's teats are sore or chapped.
- Thoroughly clean and sanitize teat dip cup before each milking.
- Use fresh teat dip for each milking. Dip solution should be changed if it becomes visibly dirty or if sediment is introduced. Do not pour used teat dip back into original container.
- Discard any teat dip sanitizing solution that becomes dirty or contaminated for any reason.
- Good dairy practices suggest the thorough cleaning and sanitizing of teats before milking to avoid contamination and assist in the control of mastitis.

PRE-DIPPING

- Remove excess organic debris and forestrip. (if water is used, use a minimal amount and dry thoroughly with clean, single-service paper towel before forestripping.)
- Dip, spray, or foam cow's teats with DeLaval QuarterMate® Plus.
- Allow a 15 - 30 second contact time.
- Dry teat thoroughly with a clean, single-service paper towel or clean, dry towel.
- Attach milker unit.

POST DIPPING

- Immediately after removing milking unit, dip or spray teats with DeLaval QuarterMate® Plus. Do not wipe.
- If outside temperature is below freezing, allow DeLaval QuarterMate® Plus to air-dry on cow's teats before cow is released outside; or allow teat dip to remain on teats for one minute, then dry teats with a single-service paper towel. Failure to follow these directions may result in frozen teats and injured animals.

Manufactured for: DeLaval, Inc.

11100 N. Congress Avenue

Kansas City, MO 64153

Phone: 816-891-7700

Manufactured by: WestAgro, Inc.,

© 2024, Made in USA

NET CONTENTS: US GAL. (L)

LOT NO.:

EXP. DATE:

PACKAGE LABEL

Add image transcription here...